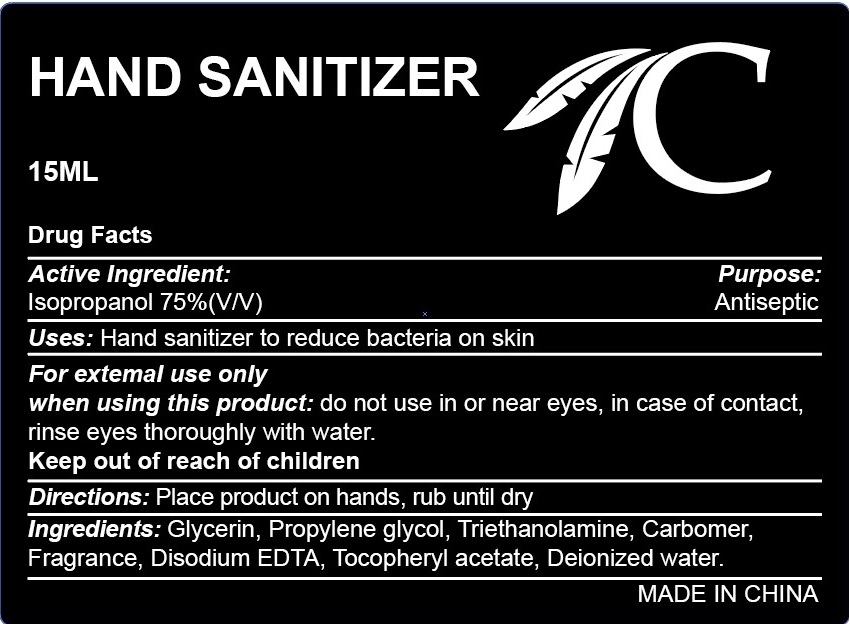 DRUG LABEL: HAND SANITIZER
NDC: 75613-013 | Form: LIQUID
Manufacturer: Ningbo Lanzi Cosmetic Technology Co., Ltd
Category: otc | Type: HUMAN OTC DRUG LABEL
Date: 20201210

ACTIVE INGREDIENTS: ISOPROPYL ALCOHOL 75 mL/100 mL
INACTIVE INGREDIENTS: WATER; PROPYLENE GLYCOL; EDETATE DISODIUM; TROLAMINE; .ALPHA.-TOCOPHEROL ACETATE, D-; GLYCERIN

HAND SANITIZER

Active ingredient

Isopropanol 75% (V/V)

Purpose

Antiseptic

Use

Hand sanitizer to reduce bacteria on skin

Warnings

For external use only

When using this product

do not use in or near eyes, in case of contact, rinse eyes thoroughly with water.

Keep out of reach of children.

If swallowed, get medical help or contact a Poison Control Center right away.

Directions

Place product on hands, rub until dry.

Inactive ingredients

Glycerin, Propylene Glycol, Triethanolamine, Carbomer, Fragrance, Disodium EDTA, Tocopheryl acetate, Deionized Water